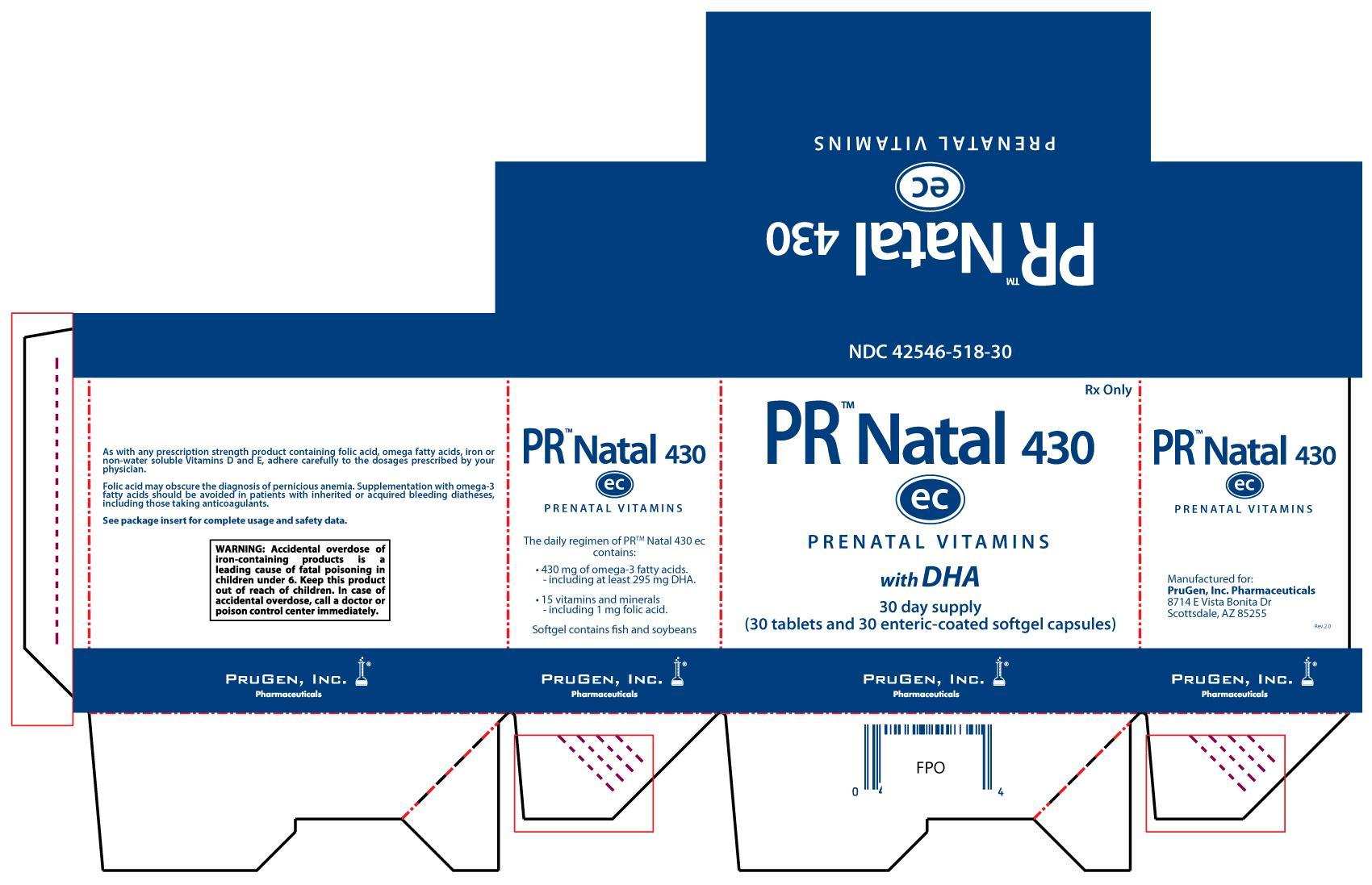 DRUG LABEL: PR Natal 430 ec
NDC: 42546-518 | Form: KIT | Route: ORAL
Manufacturer: PruGen, Inc Pharmaceuticals
Category: prescription | Type: HUMAN PRESCRIPTION DRUG LABEL
Date: 20121001

ACTIVE INGREDIENTS: BETA CAROTENE 3000 [iU]/1 1; ASCORBIC ACID 120 mg/1 1; CHOLECALCIFEROL 400 [iU]/1 1; .ALPHA.-TOCOPHEROL ACETATE, DL- 3 mg/1 1; THIAMINE MONONITRATE 1.8 mg/1 1; RIBOFLAVIN 4 mg/1 1; NIACINAMIDE 20 mg/1 1; PYRIDOXINE HYDROCHLORIDE 25 mg/1 1; FOLIC ACID 1 mg/1 1; CYANOCOBALAMIN .012 mg/1 1; CALCIUM CARBONATE 200 mg/1 1; IRON PROTEIN SUCCINYLATE 7.25 mg/1 1; FERROUS BISGLYCINATE HYDROCHLORIDE 21.75 mg/1 1; MAGNESIUM OXIDE 25 mg/1 1; ZINC OXIDE 25 mg/1 1; CUPRIC OXIDE 2 mg/1 1; OMEGA-3 FATTY ACIDS 430 mg/1 1

PR Natal 430 ec

DESCRIPTION:

PR Natal 430 ec is a prescription regimen of prenatal multi-vitamin, multi-mineral, and omega-3 fatty acid supplements, supplied as tablets and softgel capsules.

INDICATIONS:

PR Natal 430 ec is a prescription regimen of prenatal multi-vitamin, multi-mineral, and omega-3 fatty acid supplements indicated for use in improving the nutritional status of women throughout pregnancy and in the post-natal period for both lactating and non-lactating mothers. PR Natal 430 ec is also useful in improving nutritional status prior to conception.

CONTRAINDICATIONS:

This product is contraindicated in patients with known hypersensitivity to any of the ingredients including fish or fish oil.

WARNINGS: PRECAUTIONS:

Folic acid alone is improper therapy in the treatment of pernicious anemia and other megaloblastic anemias where Vitamin B12 is deficient. Since daily ingestion of more than 3 grams per day of omega-3 fatty acids (including alphalinolenic acid (ALA), eicosapentaenoic acid (EPA) and docosahexaenoic acid (DHA)) from fish oils may have potential antithrombotic activities and may increase bleeding times, administration of DHA should be avoided in patients with inherited or acquired bleeding diatheses, including those taking anticoagulants.

Folic acid especially in doses above 1.0 mg daily may obscure pernicious anemia (hematologic remission may occur while neurological manifestations remain progressive). Caution should be exercised to ensure that the prescribed dose of DHA does not exceed 1 gram (1,000 mg) per day.

WARNING:

WARNING: Accidental overdose of iron-containing products is a leading cause of fatal poisoning in children under 6. Keep this product out of reach of children. In case of accidental overdose, call a doctor or poison control center immediately.

DRUG INTERACTIONS:

Pyridoxine supplements should be avoided in patients receiving levodopa alone, as the actions of levodopa may be antagonized.

ADVERSE REACTIONS:

Allergic sensitization has been reported following both oral and parenteral administration of folic acid.

DOSAGE & ADMINISTRATION

Before, during and after pregnancy, one tablet and one softgel capsule taken by mouth daily, or as directed by a physician. The tablet and softgel capsule may be taken together or at different times of the day.

HOW SUPPLIED:

A 30-day supply of PR Natal 430 ec (NDC 42546-518-30) is supplied in 2 bottles with child-resistant caps. One bottle contains 30 pink-brown oval tablets imprinted with ‘PE 669’ on one side. A second bottle contains 30 frosted golden-colored oval enteric-coated DHA softgel capsules.

STORAGE: DISPENSING:

Store at controlled room temperature 20°-25°C (68°-77°F). Protect from moisture and excessive heat. Note that contact with moisture may produce surface discolorations of the tablet.

Keep in a well-closed, light-resistant container. Supplied in a child-resistant bottle as a safeguard against ingestion by children. KEEP THIS AND ALL MEDICATIONS OUT OF THE REACH OF CHILDREN.

Box Label

NDC 42546-518-30

PR Natal 430 ec